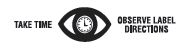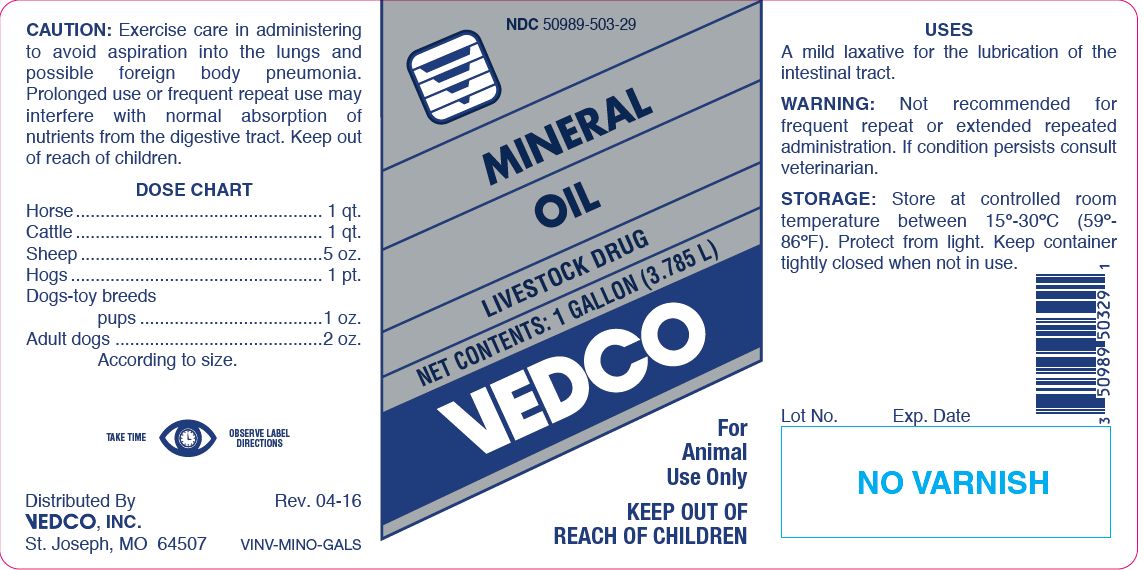 DRUG LABEL: Mineral Oil
NDC: 50989-503 | Form: LIQUID
Manufacturer: Vedco, Inc.
Category: animal | Type: OTC ANIMAL DRUG LABEL
Date: 20260219

ACTIVE INGREDIENTS: MINERAL OIL 854.5 g/1 L

MINERAL OIL

PURPOSE

LIVESTOCK DRUG

KEEP OUT OF REACH OF CHILDREN

For Animal Use Only
KEEP OUT OF REACH OF CHILDREN

CAUTION:

Exercise care in administering to avoid aspiration into the lungs and possible foreign body pneumonia. Prolonged use or frequent repeat use may interfere with normal absorption of nutrients from the digestive tract. Keep out of reach of children.

DOSE CHART

Horse.................................................. 1 qt.
Cattle .................................................. 1 qt.
Sheep .................................................5 oz.
Hogs ................................................... 1 pt.
Dogs-toy breeds
pups.....................................1 oz.
Adult dogs ..........................................2 oz.
According to size.

USES

A mild laxative for the lubrication of the intestinal tract.

WARNING:

Not recommended for frequent repeat or extended repeated administration. If condition persists consult veterinarian.

STORAGE:

Store at controlled room temperature between 15º-30ºC (59º-86ºF). Protect from light. Keep container tightly closed when not in use.

Net Contents:

One Gallon (3.785 L) VINV-MINO-GALS

INFORMATION FOR OWNERS/CAREGIVERS

Distributed By
VEDCO, INC.
St. Joseph, MO 64507